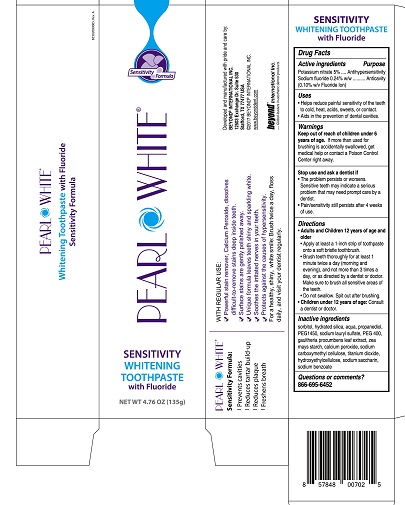 DRUG LABEL: Pearl White
NDC: 42199-006 | Form: PASTE, DENTIFRICE
Manufacturer: Beyond International Inc.
Category: otc | Type: HUMAN OTC DRUG LABEL
Date: 20231128

ACTIVE INGREDIENTS: POTASSIUM NITRATE 50 mg/1 g; SODIUM FLUORIDE 1 mg/1 g
INACTIVE INGREDIENTS: SORBITOL; HYDRATED SILICA; WATER; PROPANEDIOL; SODIUM LAURYL SULFATE; POLYETHYLENE GLYCOL 400; HYDROXYETHYL CELLULOSE (5000 MPA.S AT 1%); GAULTHERIA PROCUMBENS LEAF; SODIUM BENZOATE; TITANIUM DIOXIDE; SACCHARIN SODIUM; CALCIUM PEROXIDE; STARCH, CORN; POLYETHYLENE GLYCOL 1450; CARBOXYMETHYLCELLULOSE SODIUM

Pearl White Sensitivity Whitening Toothpaste

Drug Facts

Active ingredients

Potassium nitrate 5%
Sodium fluoride 0.24% (0.10% w/v Fluoride Ion)

Purpose

Antihypersensitivity

Anticavity

Uses

- Helps reduce painful sensitivity of the teeth to cold, heat, acids, sweets or contact.
- Aids in the prevention of dental cavities.

Warnings

Keep out of reach of children under 6 years of age. If more than used for brushing is accidentally swallowed, get medical help or contact a Poison Control Center right away.

Stop use and ask a dentist if

- The problem persists or worsens. Sensitive teeth may indicate a serious problem that may need prompt care by a dentist.
- Pain/sensitivity still persists after 4 weeks of use.

Directions

Adults and Children 12 years of age and older

- Apply at least a 1-inch strip of toothpaste onto a soft bristle toothbrush.
- Brush teeth thoroughly for at least 1 minute twice a day (morning and evening), and not more than 3 times a day, or as directed by a dentist or doctor.
- Do not swallow. Spit out after brushing.

Children under 12 years of age: Consult a dentist or doctor.

Inactive ingrediets

sorbitol, hydrated silica, aqua, propanediol, PEG1450, sodium lauryl sulfate, PEG 400, gaultheria procumbens leaf extract, zea mays starch, calcium peroxide, sodium carboxymethyl cellulose, titanium dioxide, hydroxyethylcellulose, sodium saccharin, sodium benzoate.

Questions or comments? 866-695-6452

Developed and manufactured with pride by:

BEYOND INTERNATIONAL INC.

12503 Exchange Dr. Suite 530

Stafford, TX 77477 USA

©2017 BEYOND INTERNATIONAL INC.

www.beyonddent.com

PEARL WHITE

Sensitivity Formula:

- Prevents cavities
- Reduces tartar build-up
- Reduces plaque
- Freshens breath

WITH REGULAR USE:

- Powerful stain remover, Calcium Peroxide, dissolves difficult-to-remove stains deep inside teeth.
- Surface stains are gently polished away.
- Unique formula leaves teeth shiny and sparkling white.
- Soothes the irritated nerves in your teeth.
- Protects against the causes of hypersensitivity.

For a healthy, shiny, white smile: Brush twice a day, floss daily and visit your dentist regularly.

PACKAGE LABEL

PEARL WHITE

SENSITIVITY WHITENING TOOTHPASTE

with Fluoride

NET WT. 4.76 OZ. (135 g)